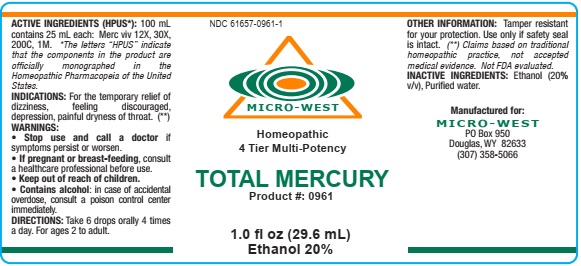 DRUG LABEL: TOTAL MERCURY
NDC: 61657-0961 | Form: LIQUID
Manufacturer: White Manufacturing Inc. DBA Micro-West
Category: homeopathic | Type: HUMAN OTC DRUG LABEL
Date: 20210121

ACTIVE INGREDIENTS: MERCURY 12 [hp_X]/30 mL
INACTIVE INGREDIENTS: ALCOHOL

DRUG FACTS

ACTIVE INGREDIENTS

MERCURIUS VIVUS [HPUS] 12X,30X,200C,1M

Contains equal volumes of each ingredient.

PURPOSE

FOR THE TEMPORARY RELIEF OF DIZZINESS, DISCOURAGED, DEPRESSION, PAINFUL DRYNESS OF THROAT

KEEP OUT OF REACH OF CHILDREN

INDICATIONS

INDICATIONS :FOR THE TEMPORARY RELIEF OF DIZZINESS,FEELING DISCOURAGED, DEPRESSION, PAINFUL DRYNESS OF THROAT

WARNING

WARNING:STOP USE AND CALL A DOCTOR IF SYMPTOMS PERSIST OR WORSEN. IF PREGNANT ORBREAST-FEEDING CONSULT A HEALTHCARE PROFESSIONAL BEFORE USE.CONTAINS ALCOHOL, IN CASE OF ACCIDENTAL OVERDOSE, CONSULT A POISON CONTROL CENTER IMMEDIATELY

DIRECTIONS

DIRECTIONS: ORALLY 6 DROPS ORALLY, 4 TIMES A DAY.FOR AGES 2 TO ADULT

INACTIVE INGREDIENT

ALCOHOL (20% V/V,PURIFIED WATER)

MANUFACTURE

MANUFACTURED FOR MICRO-WEST

DOUGLAS, WY 82633

1-307-358-5066

label

NDC 61657-0961-1

MICRO-WEST

Homeopathic

4 Tier Multi-Potency

TOTAL MERCURY

Product #: 0961

1.0 fl oz (29.6 mL)

Ethanol 20%